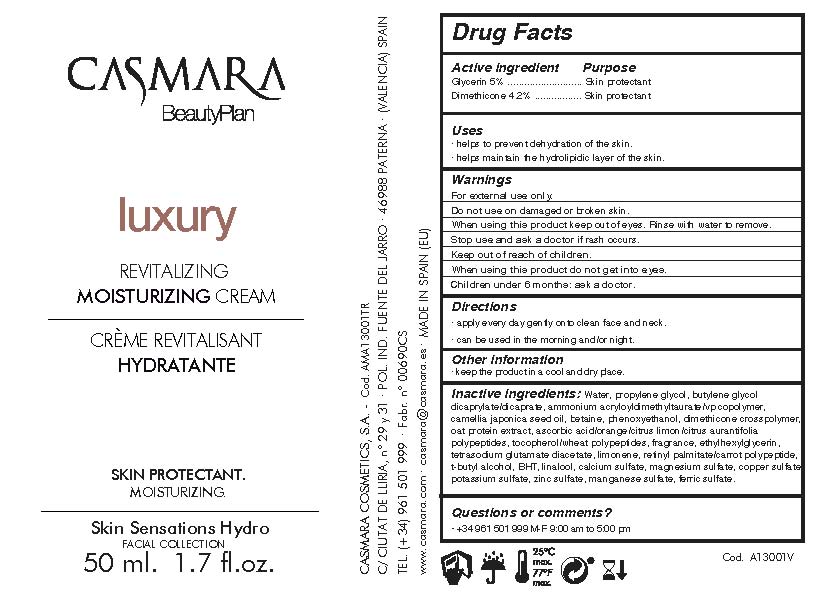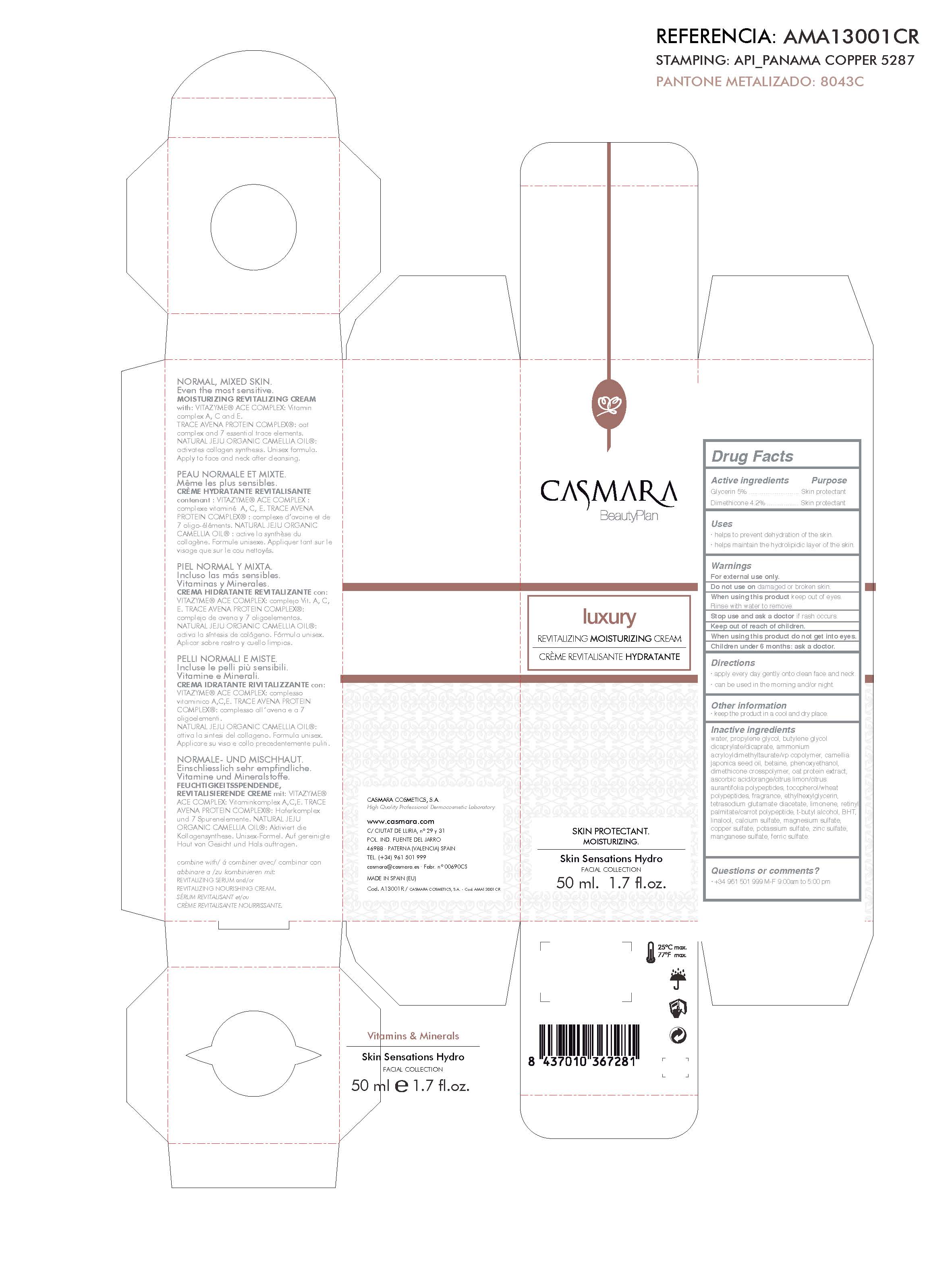 DRUG LABEL: Luxury Revitalizing Moisturizing Cream
NDC: 20151-081 | Form: CREAM
Manufacturer: Casmara Cosmetics, SA
Category: otc | Type: HUMAN OTC DRUG LABEL
Date: 20170221

ACTIVE INGREDIENTS: GLYCERIN 5 mg/1 mL; DIMETHICONE 4.2 mg/1 mL
INACTIVE INGREDIENTS: AMMONIUM ACRYLOYLDIMETHYLTAURATE/VP COPOLYMER 1417 mg/1 mL; PHENOXYETHANOL 0.9 mg/1 mL; ETHYLHEXYLGLYCERIN 0.1 mg/1 mL; TETRASODIUM GLUTAMATE DIACETATE 0.094 mg/1 mL; WATER 79.74 mg/1 mL; HYDROLYZED WHEAT PROTEIN (ENZYMATIC, 3000 MW) 0.5 mg/1 mL; DIPROPYLENE GLYCOL 2.5 mg/1 mL; BUTYLENE GLYCOL DICAPRATE 2 mg/1 mL; BETAINE 1 mg/1 mL; DIMETHICONE/DIENE DIMETHICONE CROSSPOLYMER 0.8 mg/1 mL; ASCORBIC ACID 0.33 mg/1 mL; MAGNESIUM SULFATE 0.00065 mg/1 mL; CAMELLIA JAPONICA SEED OIL 1 mg/1 mL; PERFLUNAFENE 0.1 mg/1 mL; LIMONENE, (+)- 0.03 mg/1 mL; TERT-BUTYL ALCOHOL 0.03 mg/1 mL; BUTYLATED HYDROXYTOLUENE 0.01 mg/1 mL; LINALOOL, (+)- 0.006 mg/1 mL; CALCIUM SULFATE 0.003 mg/1 mL; BASIC COPPER SULFATE 0.0005 mg/1 mL; POTASSIUM SULFATE 0.00025 mg/1 mL; ZINC SULFATE 0.00017 mg/1 mL; MANGANESE SULFATE 0.0001 mg/1 mL; FERRIC SULFATE 0.00005 mg/1 mL; VITAMIN A PALMITATE 0.031 mg/1 mL; .ALPHA.-TOCOPHEROL 0.134 mg/1 mL

LUXURY REVITALIZING MOISTURIZING CREAM

ACTIVE INGREDIENTS PURPOSE

Glycerin 5%..................... Skin Protectant

Dimethicone 4.2%............Skin Protectant

USES

. helps to prevent dehydration of the skin

. helps maintain the hydrolipidic layer of the skin

DIRECTIONS

. apply every day gently onto clean face and neck

. can be used in the morning and/or night.

DIRECTIONS

. apply every day gently onto clean face and neck

. can be used in the morning and/or night.

WARNINGS

For external use only.

Do not use on damaged or broken skin.

When using this product keep out of eyes. Rinse with water to remove.

Stop use and ask a doctor if rash occurs.

Keep out of reach of children.

When using this product do not get into eyes.

Children under 6 months: ask a doctor

WARNINGS

Children under 6 months: ask a doctor

WARNINGS

Keep out of reach of children

OTHER INFORMATION

keep the product in a cool and dry place.

INACTIVE INGREDIENTS

water, propylene glycol, butylene glycol dicaprate, ammonium acryloyldimethyltaurate/VP Copolymer, camellia japonica seed oil, betaine, phenoxyethanol, dimethicone crosspolymer, hydrolyzed wheat protein, ascorbic acid, alpha- tocopherol, perflunafene, ethylhexylglycerin, tetrasodium glutamate diacetate, limonene, Vitamina A Palmitate, tert-butyl alcohol, butylated hydroxyloluene, linaool, calcium sulfate, magnesium sulfate, copper sulfate, potassium sulfate, zinc sulfate, manganese sulfate, ferric sulfate

QUESTIONS OR COMMENTS?

+ 34 961 501 999 M-F 9:00 am to 5:00 pm